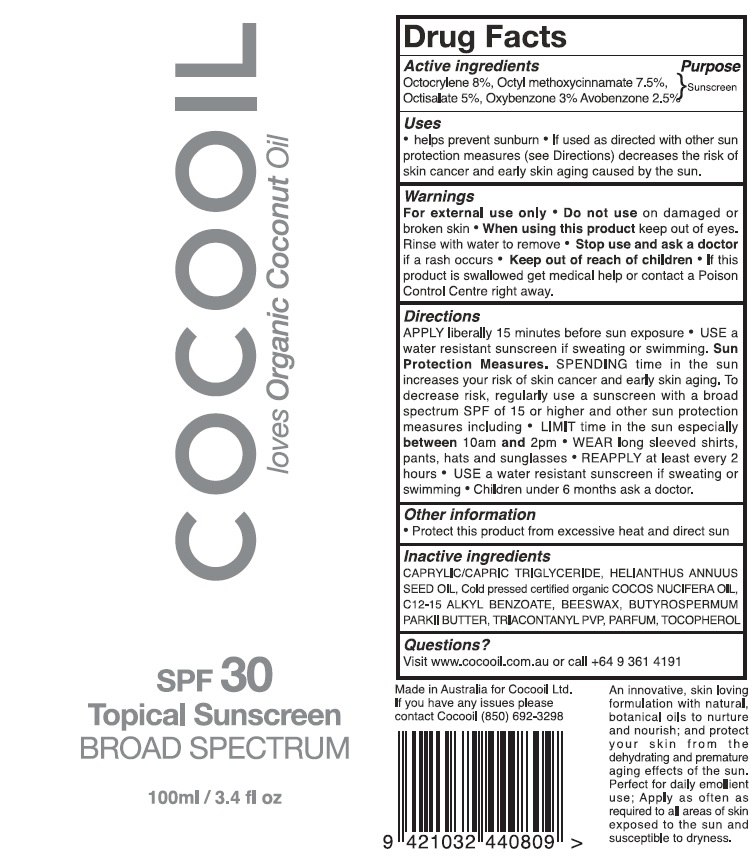 DRUG LABEL: Cocooil SPF30
NDC: 72645-002 | Form: LOTION
Manufacturer: Cocooil Limited
Category: otc | Type: HUMAN OTC DRUG LABEL
Date: 20200504

ACTIVE INGREDIENTS: OCTOCRYLENE 80 mg/1 mL; OCTINOXATE 75 mg/1 mL; OCTISALATE 50 mg/1 mL; OXYBENZONE 30 mg/1 mL; AVOBENZONE 25 mg/1 mL
INACTIVE INGREDIENTS: MEDIUM-CHAIN TRIGLYCERIDES; SUNFLOWER OIL; ALKYL (C12-15) BENZOATE; YELLOW WAX; TRICONTANYL POVIDONE; TOCOPHEROL

Cocooil SPF30

Active ingredients

Octocrylene 8%, Octyl methoxycinnamate 7.5%

Octisalate 5%, Oxybenzone 3%, Avobenzone 2.5%

Purpose

Sunscreen

Uses

- helps prevent sunburn
- If used as directed with other sun protection measures (see Directions) decreases the risk of skin cancer and early skin aging caused by the sun.

Warnings

For external use ony

Do not use

- on damaged or broken skin

When using this product

- keep out of eyes. Rinse with water to remove

Stop use and ask a doctor

- if a rash occurs

Keep out of reach of children

- If this product is swallowed get medical help or contact a Poison Control Center right away.

Directions

APPLY liberally 15 minutes before sun exposure

- USE a water resistant sunscreen if sweating or swimming. Sun Protection Measures. SPENDING time in the sun increases your risk of skin cancer and early skin aging. To decreases risk, regularly use a sunsreen with a broad spectrum SPF of 15 or higher and other sun protection measures including
- LIMIT time in the sun especially between 10am and 2pm
- WEAR long sleeved shirts, pants, hats and sunglasses
- REAPPLY at least every 2 hours
- USE a water resistant sunscreen if sweating or swimming
- Children under 6 months ask a doctor.

Other Information

- Protect this product from excessive heat and direct sun

Inactive ingrediets

CAPRYLIC/CAPROC TRIGLYCERIDE, HELIANTHUS ANNUUS SEED OIL, Cold pressed organic COCOS NUCIFERA OIL, C12-15 ALKYL BENZOATE, BEESWAX, BUTYROSPERMUM PARKII BUTTER, TRIACONTANYL PVP, PARFUM, TOCOPHEROL

Questions?

Visit www.cocooil.com.au or call +64 9 361 4191